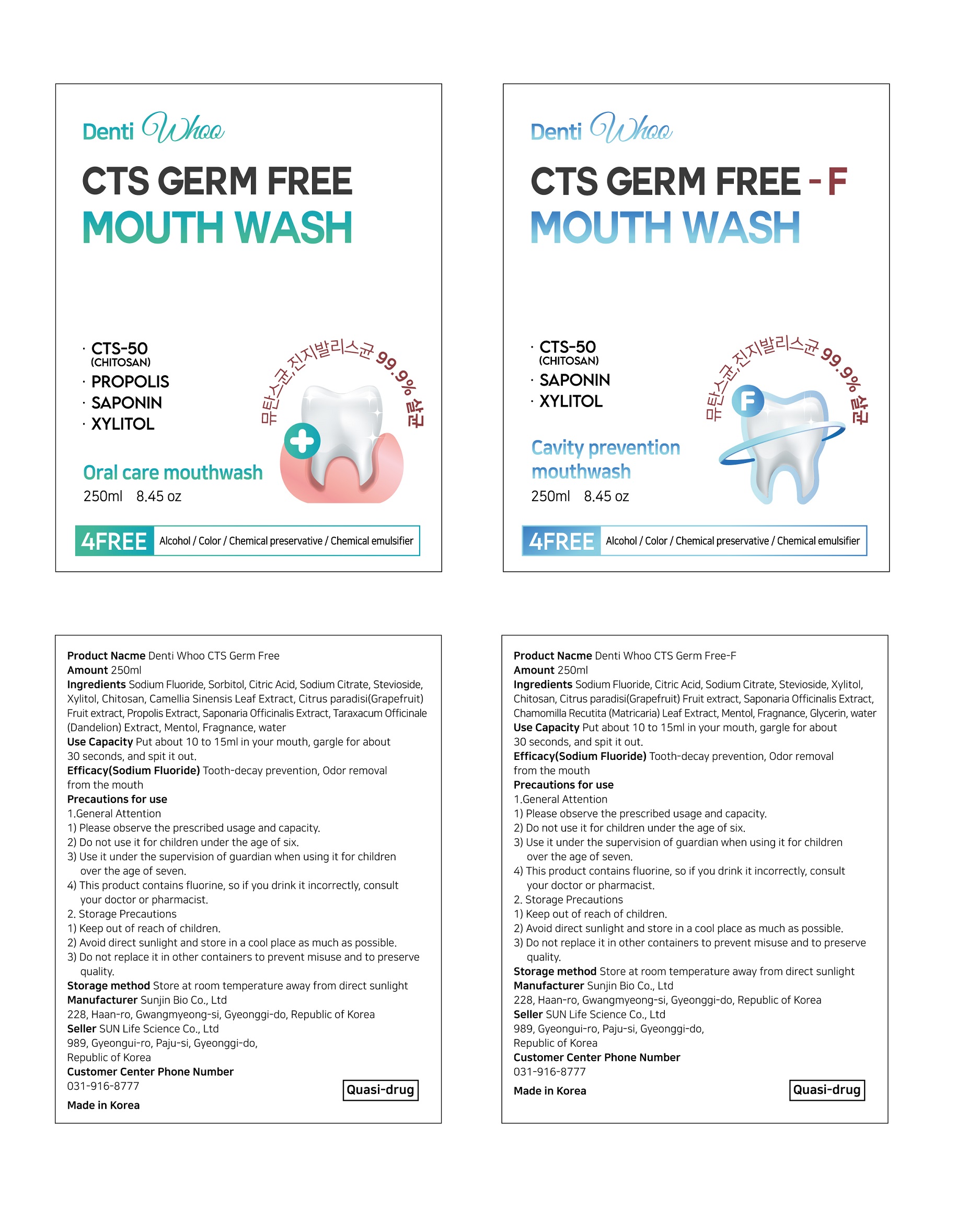 DRUG LABEL: DENTI WHOO CTS GERM FREE
NDC: 86157-0002 | Form: LIQUID
Manufacturer: SUN LIFE SCIENCE CO LTD
Category: otc | Type: HUMAN OTC DRUG LABEL
Date: 20220525

ACTIVE INGREDIENTS: SODIUM FLUORIDE 0.05 g/100 mL
INACTIVE INGREDIENTS: XYLITOL; WATER; SORBITOL

ACTIVE INGREDIENT

Sodium Fluoride

INACTIVE INGREDIENT

Sorbitol
Citric Acid
Sodium Citrate
Stevioside
Xylitol
Chitosan
Camellia Sinensis Leaf Extract
Citrus paradisi(Grapefruit) Fruit extract
Propolis Extract
Saponaria Officinalis Extract
Taraxacum Officinale (Dandelion) Extract
Mentol
Fragnance
water

PURPOSE

Tooth-decay prevention, Odor removal from the mouth

Keep out of reach of children

INDICATIONS AND USAGE

Put about 10 to 15ml in your mouth, gargle for about 30 seconds, and spit it out.

WARNINGS

1.General Attention
1) Please observe the prescribed usage and capacity.
2) Do not use it for children under the age of six.
3) Use it under the supervision of guardian when using it for children over the age of seven.
4) This product contains fluorine, so if you drink it incorrectly, consult your doctor or pharmacist.
2. Storage Precautions
1) Keep out of reach of children.
2) Avoid direct sunlight and store in a cool place as much as possible.
3) Do not replace it in other containers to prevent misuse and to preserve quality.

DOSAGE AND ADMINISTRATION

For dental use only